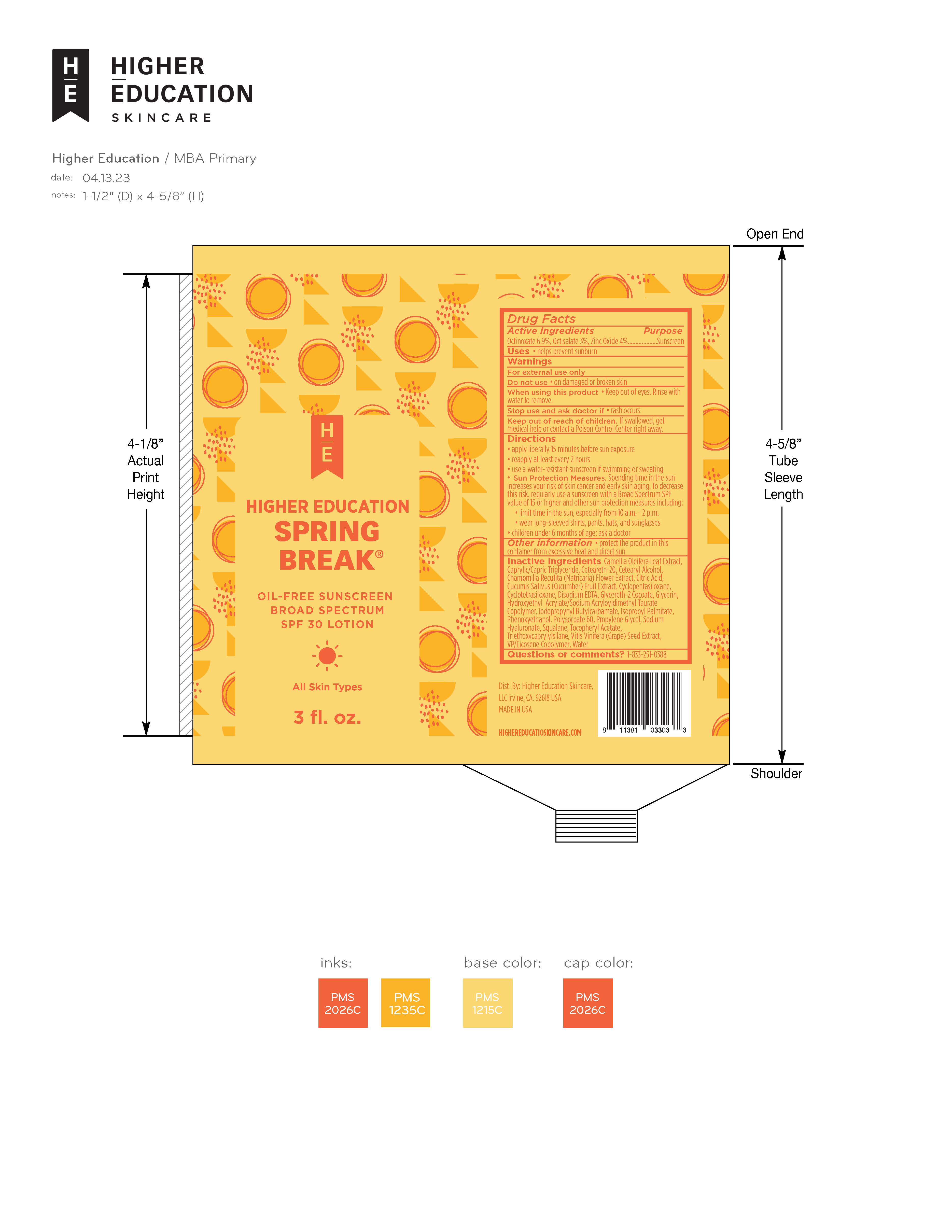 DRUG LABEL: Higher Education Spring Break Oil-Free Broad-Spectrum Sunscreen SPF 30
NDC: 72936-010 | Form: LOTION
Manufacturer: Higher Education Skincare, LLC
Category: otc | Type: HUMAN OTC DRUG LABEL
Date: 20230516

ACTIVE INGREDIENTS: OCTINOXATE 6.9 g/100 g; OCTISALATE 3 g/100 g; ZINC OXIDE 4 g/100 g
INACTIVE INGREDIENTS: TRIETHOXYCAPRYLYLSILANE; VINYLPYRROLIDONE/EICOSENE COPOLYMER; PROPYLENE GLYCOL; EDETATE DISODIUM ANHYDROUS; ISOPROPYL PALMITATE; POLYOXYL 20 CETOSTEARYL ETHER; GLYCERETH-2 COCOATE; HYDROXYETHYL ACRYLATE/SODIUM ACRYLOYLDIMETHYL TAURATE COPOLYMER (45000 MPA.S AT 1%); SQUALENE; ALPHA-TOCOPHEROL ACETATE; CITRIC ACID MONOHYDRATE; CAMELLIA OLEIFERA LEAF; PHENOXYETHANOL; HYALURONATE SODIUM; CUCUMBER; VITIS VINIFERA SEED; MEDIUM-CHAIN TRIGLYCERIDES; WATER; GLYCERIN; CETOSTEARYL ALCOHOL; CHAMOMILE; IODOPROPYNYL BUTYLCARBAMATE; CYCLOMETHICONE 4; CYCLOMETHICONE 5; POLYSORBATE 60

Higher Education SPRING BREAK Oil-Free Sunscreen SPF 30

Active Ingredients

Octinoxate 6.9%

Octisalate 3%

Zinc Oxide 4%

Uses

• helps prevent sunburn

• if used as directed with other sun protection measures (see Directions), decreases the risk of skin cancer and early skin aging caused by the sun

Warnings

For external use only

Directions

• apply a generous amount of sunscreen to your face and other exposed areas

• Wait 15 min. to let the sunscreen properly set before putting on makeup

• reapply at least every 2 hours
• use a water-resistant sunscreen if swimming or sweating
• Sun Protection Measures. Spending time in the sun increases your risk of skin cancer and early skin aging. To decrease this risk, regularly use a sunscreen with a Broad Spectrum SPF of 15 or higher and other sun protection measures including:
• limit time in the sun, especially from 10 a.m. - 2 p.m.
• wear long-sleeved shirts, pants, hats, and sunglasses
• children under 6 months of age: Ask a doctor

Inactive ingredients

Water, Glycerin, Propylene Glycol, Isopropyl Palmitate, Caprylic/Capric Triglyceride, Cyclopentasiloxane, VP/Eicosane Copolymer, Cetearyl Alcohol, Ceteareth-20, Phenoxyethanol, Hydroxyethyl Acrylate/Sodium Acryloyldimethyl Taurate Copolymer, Cyclotetrasiloxane, Squalene, Tocopheryl Acetate, Polysorbate 60, Disodium EDTA, Triethoxycaprylylsilane, Camellia Oleifera Leaf Extract, Chamomilla Recutita (Matricaria) Flower Extract, Cucumis Sativus (Cucumber) Fruit Extract, Vitis Vinifera (Grape) Seed Extract, Glycereth-2 Cocoate, Citric Acid, Sodium Hyaluronate, Iodopropynyl Butylcarbamate.

Other Information

• store at 20-25 C (68-77 F)

Questions or Comments?

1-833-251-0388

Do not use on damaged or broken skin

When using this product avoid contact with eyes. If contact occurs, rinse thoroughly with water

Stop use and ask a doctor if rash occurs

Keep out of reach of children. If product is swallowed, get medical help or contact a Poison Control Center right away.

PURPOSE

Sunscreen